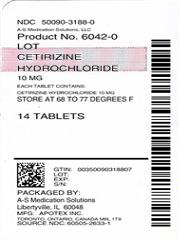 DRUG LABEL: Cetirizine Hydrochloride
NDC: 50090-3188 | Form: TABLET, FILM COATED
Manufacturer: A-S Medication Solutions
Category: otc | Type: HUMAN OTC DRUG LABEL
Date: 20190426

ACTIVE INGREDIENTS: CETIRIZINE HYDROCHLORIDE 10 mg/1 1
INACTIVE INGREDIENTS: LACTOSE MONOHYDRATE; MICROCRYSTALLINE CELLULOSE; STARCH, CORN; MAGNESIUM STEARATE; HYPROMELLOSE, UNSPECIFIED; POLYDEXTROSE; POLYETHYLENE GLYCOL 3350; TITANIUM DIOXIDE

Cetrizine HCL Tablet 10 mg

Drug Facts

Active ingredient (in each tablet)

Cetirizine HCl, USP 10 mg

Purpose

Antihistamine

Uses

temporarily relieves these symptoms due to hay fever or other upper respiratory allergies:

- runny nose
- sneezing
- itchy, watery eyes
- itching of the nose or throat

Warnings

Do not use if you have ever had an allergic reaction to this product or any of its ingredients or to an antihistamine containing hydroxyzine.

Ask a doctor before use if you have liver or kidney disease. Your doctor should determine if you need a different dose.

Ask a doctor or pharmacist before use if you are taking tranquilizers or sedatives.

When using this product

- drowsiness may occur
- avoid alcoholic drinks
- alcohol, sedatives, and tranquilizers may increase drowsiness
- be careful when driving a motor vehicle or operating machinery

Stop use and ask a doctor if an allergic reaction to this product occurs. Seek medical help right away.

WARNINGS

If pregnant or breast-feeding:

- if breast-feeding; not recommended
- if pregnant; ask a health professional before use

Keep out of reach of children. In case of overdose, get medical help or contact a Poison Control Center right away.

Directions

adults and children 6 years and over | one 10 mg tablet once daily; do not take more than one 10 mg tablet in 24 hours. A 5 mg product may be appropriate for less severe symptoms
adults 65 years and over | ask a doctor
children under 6 years of age | ask a doctor
consumers with liver or kidney disease | ask a doctor

Other information

- store between 20° and 25°C (68° - 77°F)
- USP Dissolution Test 3

Inactive ingredients

Lactose monohydrate, microcrystalline cellulose, starch (corn), magnesium stearate, hypromellose, polydextrose, polyethylene glycol and titanium dioxide.

Questions or comments?

call 1-800-706-5575, weekdays, 8:30am - 5:00pm Eastern Standard Time

Manufactured by: | Manufactured for:
Apotex Inc. | Apotex Corp.
Toronto, Ontario | Weston, Florida
Canada M9L 1T9 | 33326

HOW SUPPLIED

Product: 50090-3188

NDC: 50090-3188-0 14 TABLET, FILM COATED in a BOTTLE

NDC: 50090-3188-1 30 TABLET, FILM COATED in a BOTTLE, PLASTIC

NDC: 50090-3188-3 90 TABLET, FILM COATED in a BOTTLE, PLASTIC

NDC: 50090-3188-2 100 TABLET, FILM COATED in a BOTTLE, PLASTIC